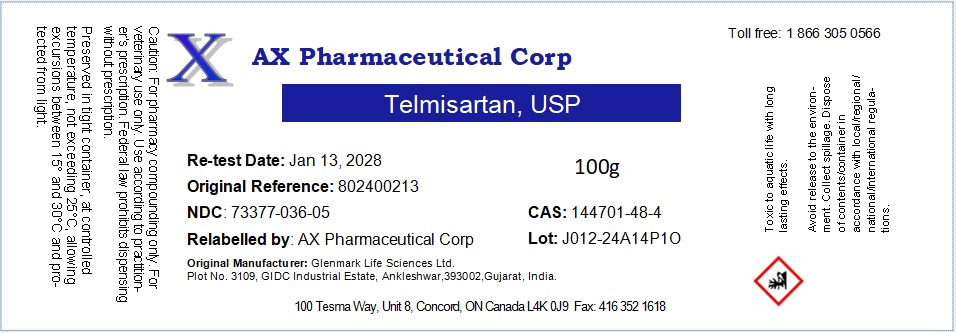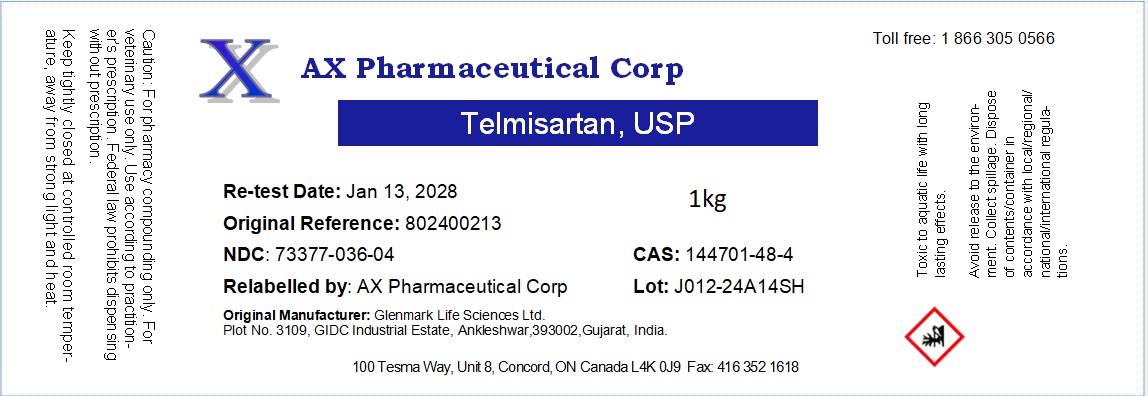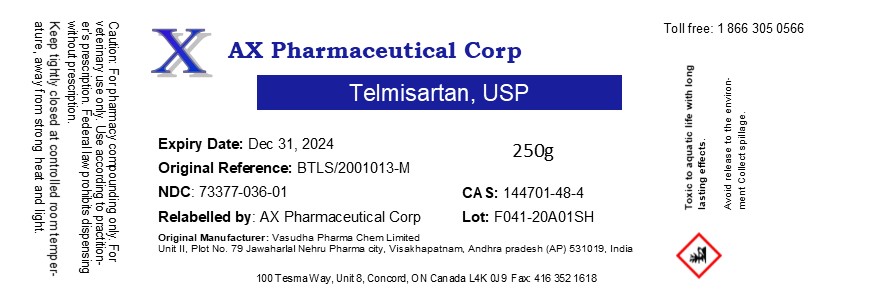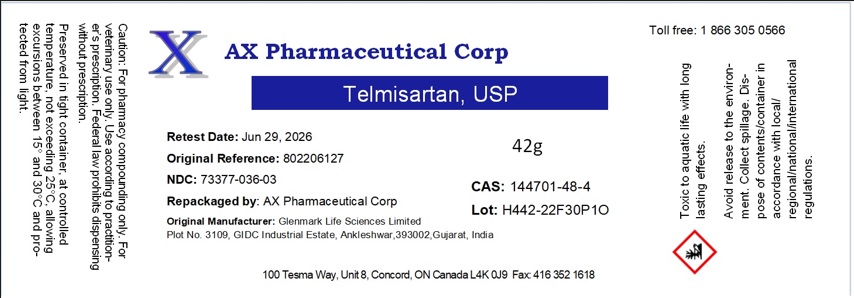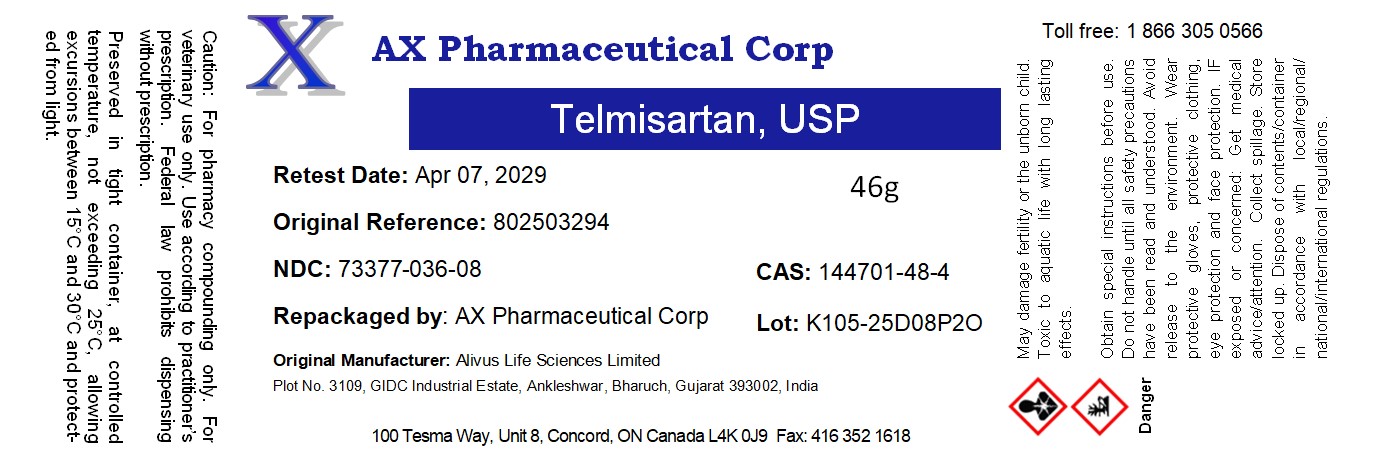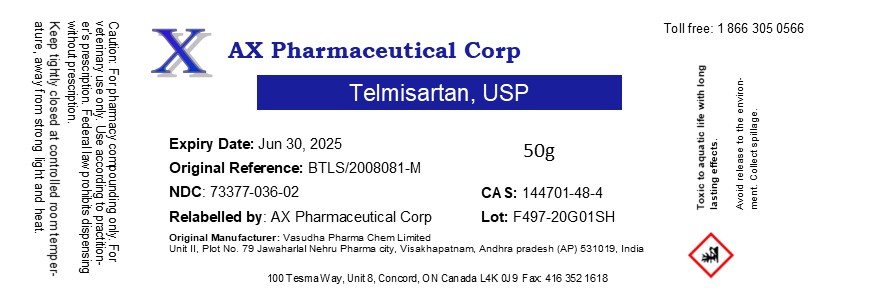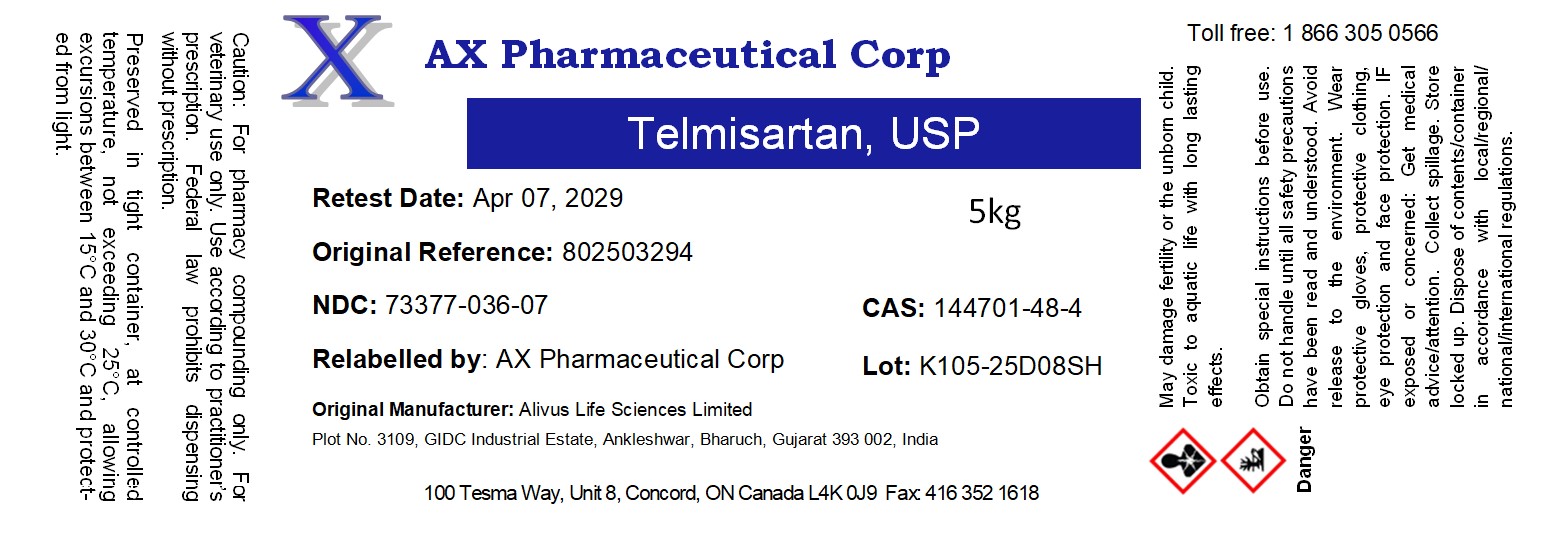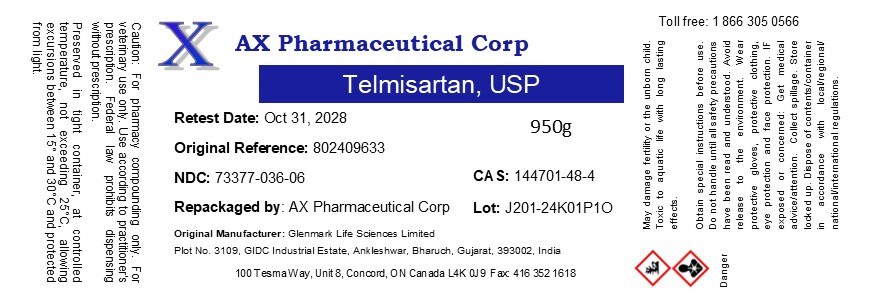 DRUG LABEL: Telmisartan
NDC: 73377-036 | Form: POWDER
Manufacturer: AX Pharmaceutical Corp
Category: other | Type: BULK INGREDIENT - ANIMAL DRUG
Date: 20260107

ACTIVE INGREDIENTS: TELMISARTAN 1 g/1 g

Telmisartan